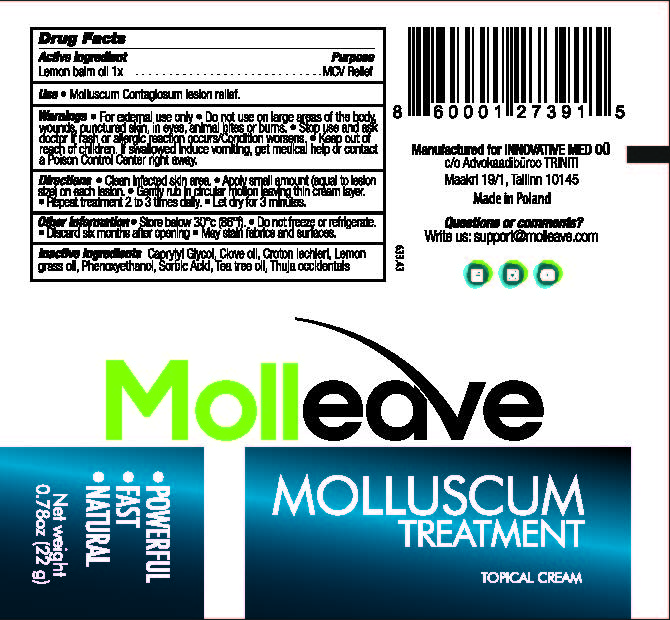 DRUG LABEL: Molleave
NDC: 73576-001 | Form: CREAM
Manufacturer: Innovative Med
Category: homeopathic | Type: HUMAN OTC DRUG LABEL
Date: 20201120

ACTIVE INGREDIENTS: LEMON BALM OIL 1 [hp_X]/22 g
INACTIVE INGREDIENTS: CLOVE OIL; CROTON LECHLERI RESIN; SORBIC ACID; TEA TREE OIL; THUJA OCCIDENTALIS LEAF; EAST INDIAN LEMONGRASS OIL; PHENOXYETHANOL; CAPRYLYL GLYCOL

Molleave (Innovative Med)

Active Ingredients

Active Ingredient Purpose

Lemon balm oil 1x............................................MCV Relief

Purpose

MCV Relief

Use

- Molluscum Contagiosum lesion relief.

Warnings

- For external use only
- Do not use on large areas of the body, wounds, punctured skin, in eyes, animal bites or burns.
- Stop use and ask doctor if rash or allergic reaction occurs/Condition worsens.
- If swallowed induce vomiting, get medical help or contact a Poison Control Center right away.

Keep out of reach of children.

Directions

- Clean infected skin area.
- Apply small aount (equal to lesion size) on each lesion.
- Gently rub in circular motion leaving thin cream layer.
- Repeat treatment 2 to 3 times daily.
- Let dry for 3 minutes.

Other Information

- Store below 30 degrees C (86 degrees F)
- Do not freeze or refrigerate
- Discard six months after opening
- May stain fabrics and surfaces

Inactive Ingredients

Inactive Ingredients Caprylyl Glycol, Clove oil, Croton lechleri, Lemon grass oil, phenoxyethanol, sorbic acid, tea tree oil, thuja occidentalis

Inactive Ingredients

Inactive Ingredients Caprylyl Glycol, Clove oil, Croton lechleri, Lemon grass oil, phenoxyethanol, sorbic acid, tea tree oil, thuja occidentalis